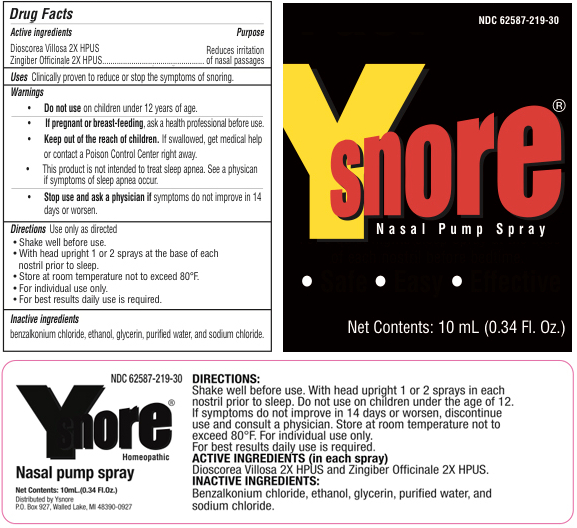 DRUG LABEL: YSNORE
NDC: 62587-219 | Form: SPRAY
Manufacturer: Y Snore
Category: homeopathic | Type: HUMAN OTC DRUG LABEL
Date: 20180109

ACTIVE INGREDIENTS: DIOSCOREA VILLOSA ROOT 2 [hp_X]/1 mL; GINGER 2 [hp_X]/1 mL
INACTIVE INGREDIENTS: BENZALKONIUM CHLORIDE; ALCOHOL; GLYCERIN; WATER; SODIUM CHLORIDE

YSNORE Anti-Snoring Nasal Pump Spray 10ml

Homeopathic Purpose

Active Ingredients | Purpose
Dioscorea Villosa 2x HPUS | Reduces irritation of nasal Passages
Zingiber Officianle 2x HPUS | ....

Uses

Clinically proven to reduce or stop the symptoms of snoring.

Warnings

• Do not use on children under 12 years of age.

PREGNANCY OR BREAST FEEDING

• If pregnant or breast-feeding, ask a health professional before use.

KEEP OUT OF REACH OF CHILDREN

• Keep out of the reach of children. If swallowed, get medical help or contact a Poison Control Center right away.

WARNINGS

• This product is not intended to treat sleep apnea. See a physician if symptoms of sleep apnea occur.

• Stop use and ask a physician if symptoms do not improve in 14 days, or worsen.

Directions

Use only as directed
• Shake well before use.
• With head upright 1 or 2 sprays at the base of each nostril prior to sleep.
• Store at room temperature not to exceed 80° F.
• For individual use only.
• For best results daily use is required.

Inactive Ingredients

benzalkonium chloride, ethanol, glycerin, purified water, and sodium chloride.

PACKAGE LABEL

Updated 1/9/2108